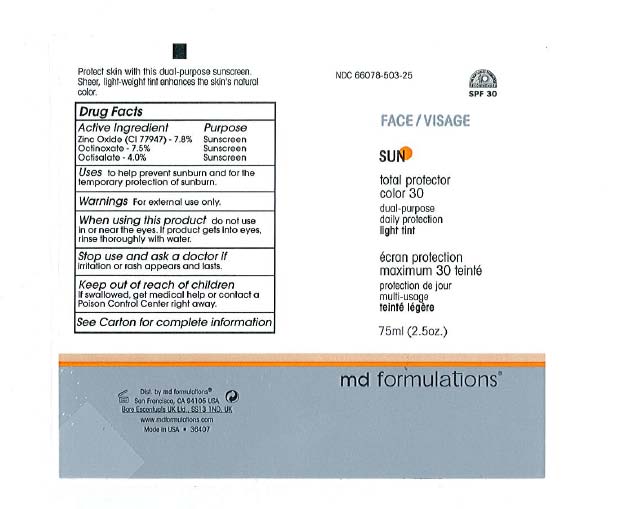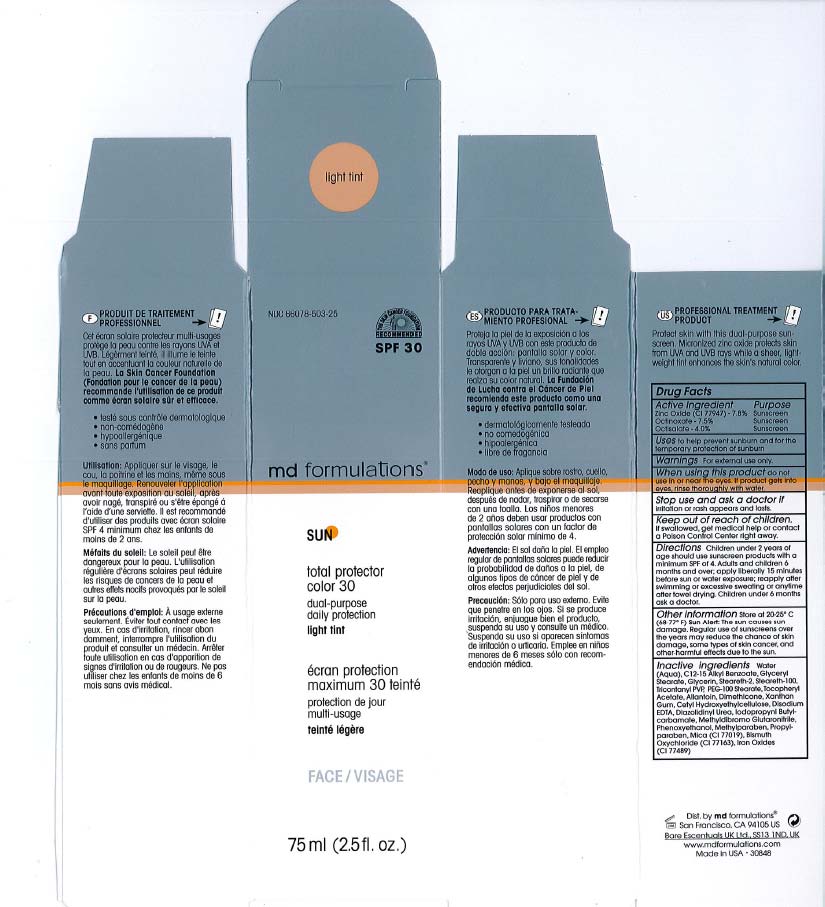 DRUG LABEL: Sun Total Protector Color 30 Light Tint
NDC: 66078-503 | Form: CREAM
Manufacturer: MD Formulations
Category: otc | Type: HUMAN OTC DRUG LABEL
Date: 20100817

ACTIVE INGREDIENTS: Zinc Oxide 7.8 mL/100 mL; Octisalate 4 mL/100 mL; Octinoxate 7.5 mL/100 mL

Total Protector Color 30 light tint

ACTIVE INGREDIENT

Zinc Oxide - 7.8%
Octlnoxate - 7.5%
Octlsolote - 4.0%

PURPOSE

Zinc Oxide - 7.8% Sunscreen
Octlnoxate - 7.5% Sunscreen
Octlsolote - 4.0% Sunscreen

When using this product do not use in or near the eyes. If product gets into eyes, rinse thoroughly with water.

INDICATIONS AND USAGE

Uses to help prevent sunburn and for the temporary protection of sunburn.

Warnings : For external use only.

Stop use and ask a doctor if irritation or rash appears and lasts.

Keep out of reach of children. If swallowed, get medical help or contact a Poison Control Center right away.

DOSAGE AND ADMINISTRATION

Children under 2 years of age should use sunscreen products with a minimum SPF of 4. Adults and children 6 months and over; apply liberally 15 minutes before sun or water exposure; reapply after swimming or excessive sweating or anytime after towel drying. Children under 6 months ask a doctor.

Other information Store at 20-25C (68 - 77F) Sun Alert: The sun causes sun damage. Regular use of sunscreens over the years may reduce the chance of skin damage, some types of skin cancer, and other harmful effects due to the sun.

INACTIVE INGREDIENT

Inactive ingredients: Water (Aqua), C12-15 Alkyl Benzoate, Glyceryl Stearate, Glycerin, Stearelh·2, Stearelh-100, Trlcontanyl PVP, PEG-100 stearate, Tocopheryl Acetate, Allantoin, Dimethicone, Xanthan Gum, Cetyl Hydroxyethylcellulose, Disodium EDTA, Diazolidinyl Urea, lodopropynl Butylcarbamate, Methyldibromo Glutaronitrile, Phenoxyethanol, Methylparaben, Propylparaben, MIca (CI 77019), Blsmuth OxychlorIde (CI 77163), Iron Oxides (CI77489)